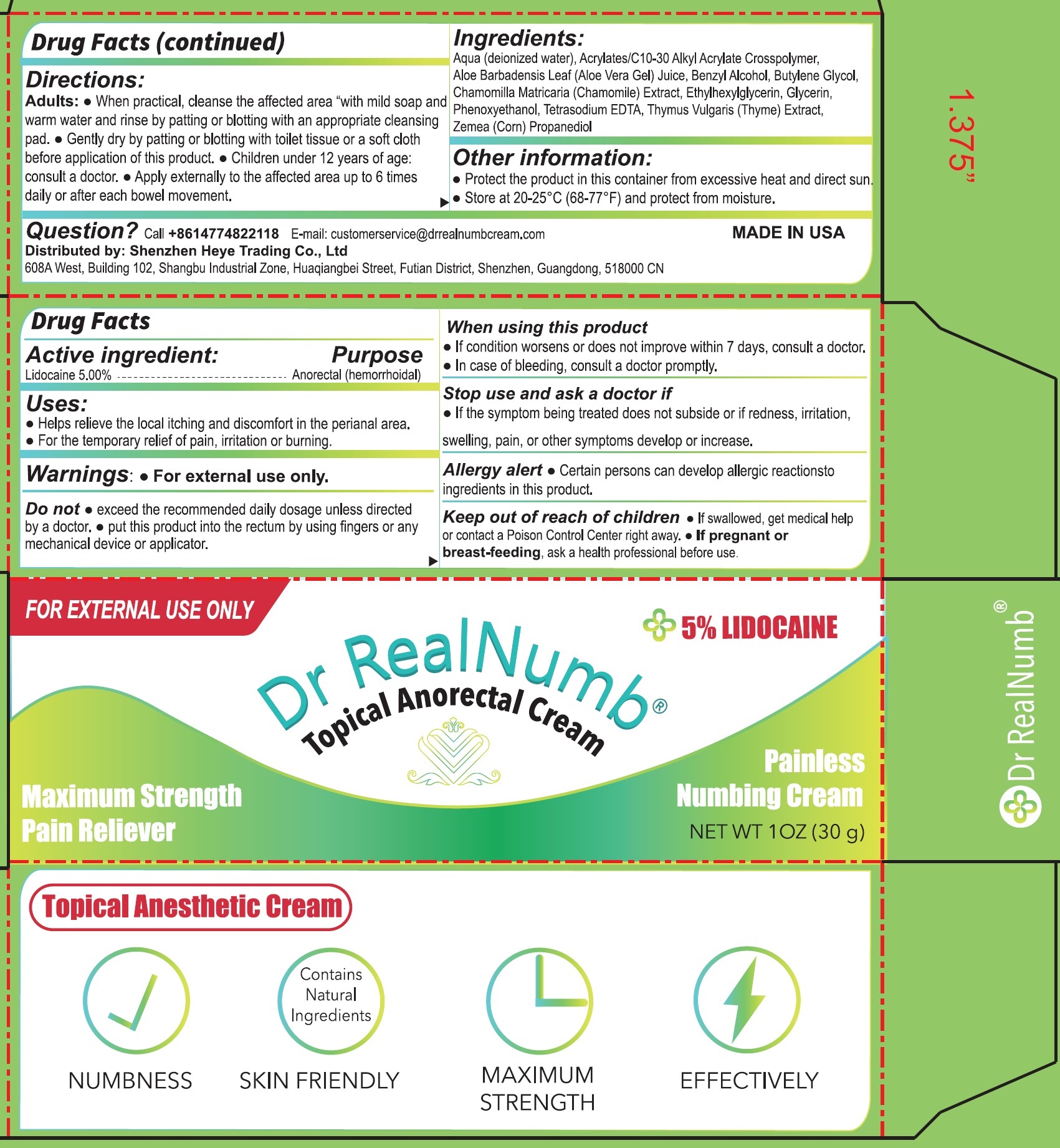 DRUG LABEL: DR REAL NUMB Topical Anorectal
NDC: 83800-430 | Form: CREAM
Manufacturer: FUZZYLULU LLC
Category: otc | Type: HUMAN OTC DRUG LABEL
Date: 20231109

ACTIVE INGREDIENTS: LIDOCAINE 50 mg/1 g
INACTIVE INGREDIENTS: WATER; ACRYLATES/C10-30 ALKYL ACRYLATE CROSSPOLYMER (60000 MPA.S); ALOE VERA LEAF; BENZYL ALCOHOL; BUTYLENE GLYCOL; CHAMOMILE; ETHYLHEXYLGLYCERIN; GLYCERIN; PHENOXYETHANOL; EDETATE SODIUM; THYME; CORN

DR REAL NUMB Topical Anorectal Cream

Active ingredient

Lidocaine 5.00%

Purpose

Anorectal (hemorrhoidal)

Uses:

- Helps relieve the local itching and discomfort in the perianal area.
- For the temporary relief of pain, irritation or burning.

Warnings:

- For external use only.

Do not

- exceed the recommended daily dosage unless directed by a doctor.
- put this product into the rectum by using fingers or any mechanical device or applicator.

When using this product

- If condition worsens or does not improve within 7 days, consult a doctor.
- In case of bleeding, consult a doctor promptly.

Stop use and ask a doctor if

- If the sympton being treated does not subside or if redness, irritation, swelling, pain, or other symptoms develop or increase.

Allergy alert

- Certain persons can develop allergic reactions to ingredients in this product.

keep out of reach of children

- If swallowed, get medical help or contact a Poison Control Center right away.

If pregnant or breast-feeding,

ask a health professional before use.

Directions:

Adults:

- When practical, cleanse the affected area "with mild soap and warm water and rinse by patting or blotting with an appropriate cleansing pad.
- Gently dry by patting or blotting with an appropriate cleansing pad.
- Children under 12 years of age: consult a doctor.
- Apply externally to the affected area up to 6 times daily or after each bowel movement.

Ingredients:

Aqua (deionized water), Acrylates/C10-30 Alkyl Acrylate Crosspolymer, Aloe Barbadensis Leaf (Aloe Vera Gel) Juice, Benzyl Alochol, Butylene Glycol, Chamomilla Matricaria (Chamomile) Extract, Ethylhexylglycyerin, Glycerin, Phenoxyethanol, Tetrasodium EDTA, Thymus Vulgaris (Thyme) Extract, Zemea (corn) Propanediol.

Other information:

- Protect the product in this container from excessive heat and direct sun.
- Store at 20-25°C (68-77°F) and protect from moisture.

Question?

Call + 8614774822118

E-mail: customerservice@drrealnumbcream.com